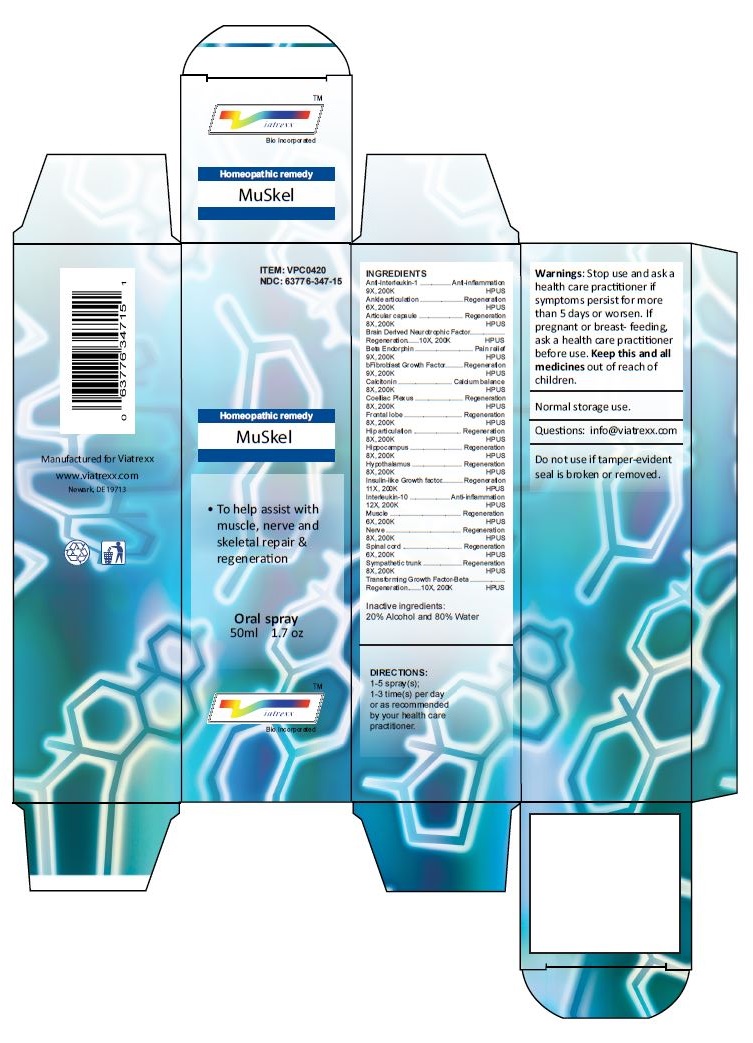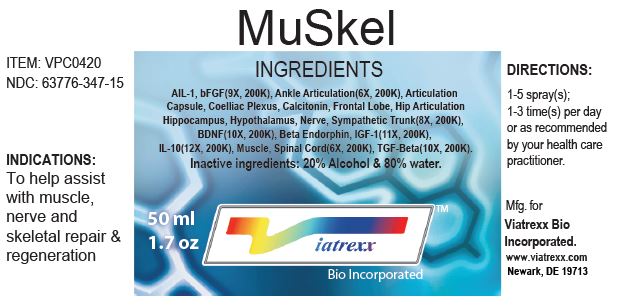 DRUG LABEL: MuSkel
NDC: 63776-347 | Form: SPRAY
Manufacturer: VIATREXX BIO INCORPORATED
Category: homeopathic | Type: HUMAN OTC DRUG LABEL
Date: 20221130

ACTIVE INGREDIENTS: SUS SCROFA HIP JOINT 200 [kp_C]/1 mL; BOS TAURUS HIPPOCAMPUS 200 [kp_C]/1 mL; SUS SCROFA HIPPOCAMPUS 200 [kp_C]/1 mL; BOS TAURUS HYPOTHALAMUS 200 [kp_C]/1 mL; SUS SCROFA HYPOTHALAMUS 200 [kp_C]/1 mL; MECASERMIN RINFABATE 200 [kp_C]/1 mL; INTERLEUKIN-10 200 [kp_C]/1 mL; BEEF 200 [kp_C]/1 mL; PORK 200 [kp_C]/1 mL; BOS TAURUS NERVE 200 [kp_C]/1 mL; SUS SCROFA NERVE 200 [kp_C]/1 mL; BOS TAURUS SPINAL CORD 200 [kp_C]/1 mL; SUS SCROFA SPINAL CORD 200 [kp_C]/1 mL; BOS TAURUS SYMPATHETIC NERVE 200 [kp_C]/1 mL; SUS SCROFA SYMPATHETIC NERVE 200 [kp_C]/1 mL; TRANSFORMING GROWTH FACTOR BETA-1 200 [kp_C]/1 mL; ANTI-INTERLEUKIN-1.ALPHA. IMMUNOGLOBULIN G RABBIT 200 [kp_C]/1 mL; BOS TAURUS ANKLE JOINT 200 [kp_C]/1 mL; SUS SCROFA ANKLE JOINT 200 [kp_C]/1 mL; BOS TAURUS JOINT CAPSULE 200 [kp_C]/1 mL; SUS SCROFA JOINT CAPSULE 200 [kp_C]/1 mL; BRAIN-DERIVED NEUROTROPHIC FACTOR HUMAN 200 [kp_C]/1 mL; METENKEFALIN 200 [kp_C]/1 mL; ERSOFERMIN 200 [kp_C]/1 mL; BOS TAURUS SOLAR PLEXUS 200 [kp_C]/1 mL; SUS SCROFA SOLAR PLEXUS 200 [kp_C]/1 mL; CALCITONIN 200 [kp_C]/1 mL; BOS TAURUS FRONTAL LOBE 200 [kp_C]/1 mL; SUS SCROFA FRONTAL LOBE 200 [kp_C]/1 mL; BOS TAURUS HIP JOINT 200 [kp_C]/1 mL
INACTIVE INGREDIENTS: ALCOHOL; WATER

MuSkel

Active Ingredients

Anti-Interleukin-1 9 9X 200K, Ankle articulation 6X 200K, Articular capsule 8X 200K, Brain Derived Neurotrophic Factor 10X 200K, Beta Endorphin 9X 200K, bFibroblast Growth Factor 9X 200K, Coelliac Plexus 8X 200K,Calcitonin 8X 200K, Frontal lobe 8X 200K, Hip articulation 8X 200K, Hippocampus 8X 200K, Hypothalamus 8X 200K, Insulin-like Growth factor 11X 200K, Interleukin-10 12X 200K, Muscle 6X 200K, Nerve 8X 200K, Spinal cord 6X 200K, Sympathetic trunk 8X 200K, Transforming Growth Factor-Beta 10X 200K,

Purpose

Anti-Interleukin-1 | Anti-inflammation
Ankle articulation | Regeneration
Articular capsule | Regeneration
Brain Derived Neurotrophic Factor | Regeneration
Beta Endorphin | Pain relief
bFibroblast Growth Factor | Regeneration
Coelliac Plexus | Regeneration
Calcitonin | Calcium balance
Frontal lobe | Regeneration
Hip articulation | Regeneration
Hippocampus | Regeneration
Hypothalamus | Regeneration
Insulin-like Growth factor | Regeneration
Interleukin-10 | Anti-inflammation
Muscle | Regeneration
Nerve | Regeneration
Spinal cord | Regeneration
Sympathetic trunk | Regeneration
Transforming Growth Factor-Beta | Regeneration

Uses

To help assist with muscle, nerve and skeletal repair & regeneration

Warnings

Stop use and ask a health care practitioner if symptoms persist for more than five days or worsen. If pregnant or breastfeeding, ask a health care practitioner before use.

Dosage

1-5 spray(s); 1-3 time(s) per day or as recommended by your health care practitioner.

KEEP OUT OF REACH OF CHILDREN

Keep this and all medicines out of reach of children.

Other Ingredients

Alcohol and Water

Other Information

Normal storage use.
Do not use if tamper-evident seal is broken or removed.

Questions

info@viatrexx.com

Principal Display Panel

ITEM: VPC0420
NDC 63776-347-15
Homeopathic remedy
MuSkel
• To help assist with muscle, nerve and skeletal repair & regeneration
Oral spray
50ml 1.7 oz
Viatrexx™ Bio Incorporated
Manufactured by Viatrexx
www.viatrexx.com
Newark, DE 19713

MuSkel
50 mL
1.7 oz
Viatrexx™ Bio Incorporated
ITEM: VPC0420
NDC: 63776-347-15
INDICATIONS:
To help assist with muscle, nerve and skeletal repair & regeneration
DIRECTIONS:
1-5 spray(s); 1-3 time(s) per day or as recommended by your health care practitioner.
Mfg. for
Viatrexx Bio Inccorporated.
www.viatrexx.com
Newark, DE 19713